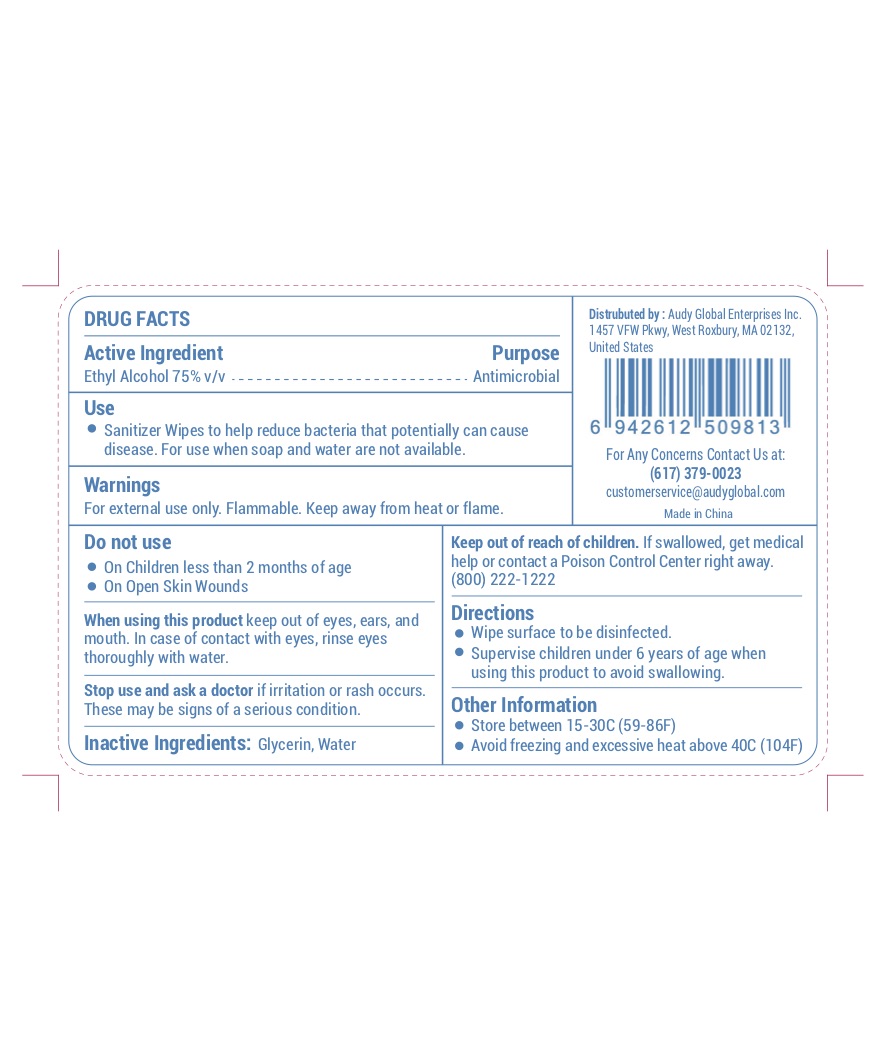 DRUG LABEL: Hand Sanitizer Wipes
NDC: 75778-002 | Form: SOLUTION
Manufacturer: Audy Global Enterprises Inc.
Category: otc | Type: HUMAN OTC DRUG LABEL
Date: 20200428

ACTIVE INGREDIENTS: ALCOHOL 75 1/100 1
INACTIVE INGREDIENTS: WATER 24.8 1/100 1; GLYCERIN 0.2 1/100 1

Active Ingredient(s)

Ethyl Alcohol 75% v/v. Purpose: Antimicrobial

Purpose: Antimicrobial

Use

Sanitizer Wipes to help reduce bacteria that potentially can cause disease. For use when soap and water are not available.

Warnings

For external use only. Flammable. Keep away from heat or flame

Do not use

- in children less than 2 months of age
- on open skin wounds

When using this product keep out of eyes, ears, and mouth. In case of contact with eyes, rinse eyes thoroughly with water.
Stop use and ask a doctor if irritation or rash occurs. These may be signs of a serious condition.
Keep out of reach of children. If swallowed, get medical help or contact a Poison Control Center right away. (800)222-1222

Stop use and ask a doctor if irritation or rash occurs. These may be signs of a serious condition.

Keep out of reach of children. If swallowed, get medical help or contact a Poison Control Center right away.

Directions

- Wipe surface to be disinfected.
- Supervise children under 6 years of age when using this product to avoid swallowing.

Other information

- Store between 15-30C (59-86F)
- Avoid freezing and excessive heat above 40C (104F)

Inactive ingredients

Glycerin, Water

Package Label - Principal Display Panel

500 ml NDC: 75778-002-60